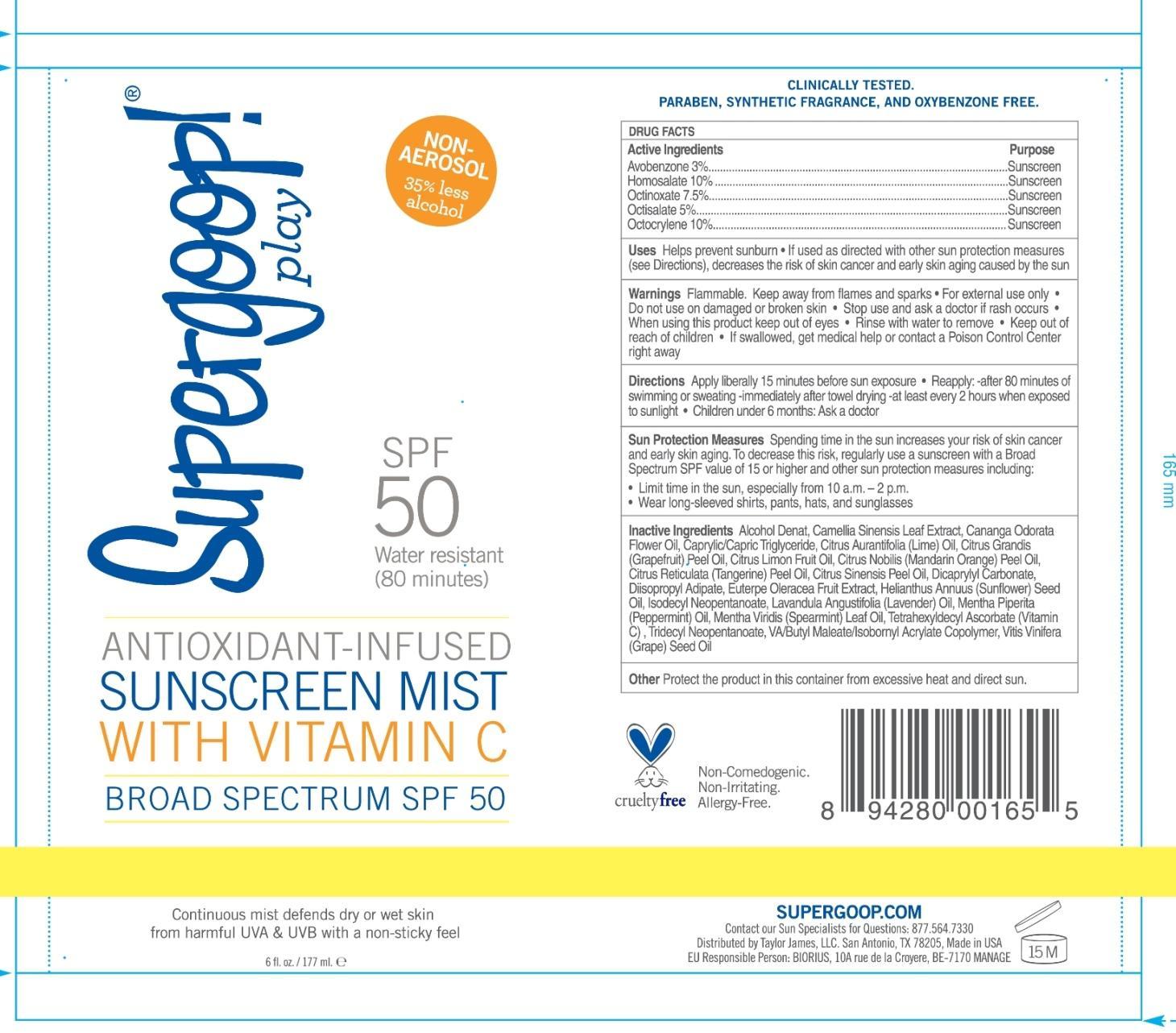 DRUG LABEL: Sunscreen Mist Broad Spectrum SPF 50
NDC: 75936-124 | Form: SPRAY
Manufacturer: TAYLOR JAMES, LTD.
Category: otc | Type: HUMAN OTC DRUG LABEL
Date: 20170105

ACTIVE INGREDIENTS: AVOBENZONE 3 g/100 mL; HOMOSALATE 10 g/100 mL; OCTINOXATE 7.5 g/100 mL; OCTISALATE 5 g/100 mL; OCTOCRYLENE 10 g/100 mL
INACTIVE INGREDIENTS: GREEN TEA LEAF; CANANGA OIL; MEDIUM-CHAIN TRIGLYCERIDES; LIME OIL; CITRUS MAXIMA FRUIT RIND OIL; CITRUS LIMON FRUIT OIL; MANDARIN OIL; ORANGE OIL TERPENELESS; DICAPRYLYL CARBONATE; DIISOPROPYL ADIPATE; ACAI; SUNFLOWER OIL; ISODECYL NEOPENTANOATE; LAVENDER OIL; PEPPERMINT OIL; SPEARMINT OIL; TETRAHEXYLDECYL ASCORBATE; TRIDECYL NEOPENTANOATE; GRAPE SEED OIL

Sunscreen Mist Broad Spectrum SPF 50

Active Ingredients Purpose
Avobenzone 3% Sunscreen

Homosalate 10% Sunscreen

Octinoxate 7.5% Sunscreen

Octisalate 5% Sunscreen

Octocrylene 10% Sunscreen

PURPOSE

Uses Helps prevent sunburn

If used as directed with other sun protection measures (see directions), decreases the risk of skin cancer and early skin aging caused by the sun

Keep out of reach of children

Stop use and ask a doctor if rash occurs

Warnings Flammable. Keep away from flames and sparks

For external use only.

Do not use on damaged or broken skin.

When using this product, keep out of eyes. Rinse with water to remove.

If swallowed, get medical help or contact a Poison Control Center right away.

Directions

Apply liberally 15 minutes before sun exposure

Reapply:

after 80 minutes of swimming or sweating

immediately after towel drying

at least every 2 hours when exposed to sunlight

Children under 6 months: Ask a doctor

INACTIVE INGREDIENT

Inactive Ingredients Alcohol Denat , Camellia Sinensis Leaf Extract, Cananga Odorata Flower Oil, Caprylic/Capric triglyceride, Citrus Aurantifolia (Lime) Oil, Citrus Grandis (Grapefruit) Peel Oil, Citrus Limon Fruit Oil, Citrus Nobilis (Mandarin Orange) Peel Oil, Citrus Reticulata (Tangerine) Peel Oil, Citrus Sinensis Peel Oil, Dicaprylyl Carbonate, Diisopropyl Adipate, Euterpe Oleracea Fruit Extract, Helianthuus Annuus (Sunflower) Seed Oil, Isodecyl Neopentanoate, Lavandula Angustifolia Mentha Piperita (Peppermint) Oil, Mentha Viridis (Spearmint) Leaf Oil, Tetrahexyldecyl Ascorbate (vitamin C), Tridecyl Neopentanoate, VA/Butyl Maleate/Isobornyl Acrylate Copolymer, Vitis Vinifera (Grape) Seed Oil.

PACKAGE LABEL

Water resistant (80 minutes)

Apply to wet or dry skin

twist-lock cap

SPF 50 sunscreen

Antioxidant-Infused

Sunscreen Mist

with Vitamin C

Broad Spectrum